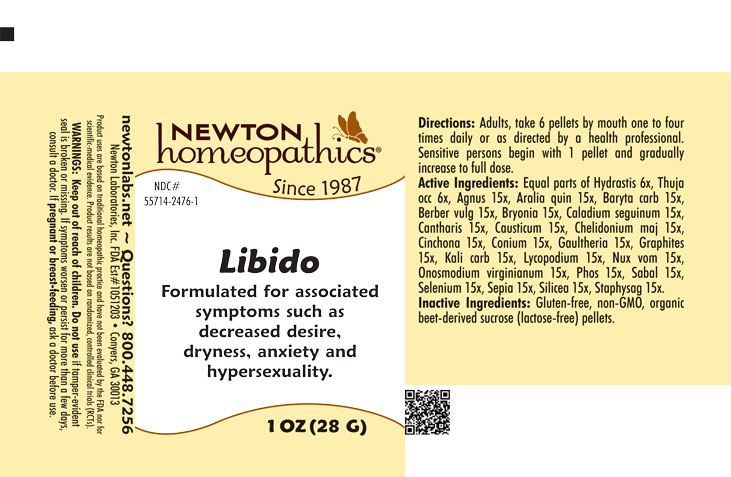 DRUG LABEL: Libido
NDC: 55714-2476 | Form: PELLET
Manufacturer: Newton Laboratories, Inc.
Category: homeopathic | Type: HUMAN OTC DRUG LABEL
Date: 20250919

ACTIVE INGREDIENTS: SEPIA OFFICINALIS JUICE 15 [hp_X]/1 g; DELPHINIUM STAPHISAGRIA SEED 15 [hp_X]/1 g; GOLDENSEAL 6 [hp_X]/1 g; CHASTE TREE FRUIT 15 [hp_X]/1 g; AMERICAN GINSENG 15 [hp_X]/1 g; BARIUM CARBONATE 15 [hp_X]/1 g; LYTTA VESICATORIA 15 [hp_X]/1 g; BERBERIS VULGARIS ROOT BARK 15 [hp_X]/1 g; BRYONIA ALBA ROOT 15 [hp_X]/1 g; DIEFFENBACHIA SEGUINE 15 [hp_X]/1 g; CAUSTICUM 15 [hp_X]/1 g; CHELIDONIUM MAJUS 15 [hp_X]/1 g; CINCHONA OFFICINALIS BARK 15 [hp_X]/1 g; CONIUM MACULATUM FLOWERING TOP 15 [hp_X]/1 g; GAULTHERIA PROCUMBENS TOP 15 [hp_X]/1 g; GRAPHITE 15 [hp_X]/1 g; POTASSIUM CARBONATE 15 [hp_X]/1 g; LYCOPODIUM CLAVATUM SPORE 15 [hp_X]/1 g; STRYCHNOS NUX-VOMICA SEED 15 [hp_X]/1 g; ONOSMODIUM VIRGINIANUM 15 [hp_X]/1 g; PHOSPHORUS 15 [hp_X]/1 g; SAW PALMETTO 15 [hp_X]/1 g; SELENIUM 15 [hp_X]/1 g; THUJA OCCIDENTALIS LEAFY TWIG 6 [hp_X]/1 g; SILICON DIOXIDE 15 [hp_X]/1 g
INACTIVE INGREDIENTS: SUCROSE

Libido 2476P

INDICATIONS & USAGE SECTION

Formulated for associated symptoms such as decreased desire, dryness, anxiety and hypersexuality.

DOSAGE & ADMINISTRATION SECTION

Directions: Adults, take 6 pellets by mouth one to four times daily or as directed by a health professional. Sensitive persons begin with 1 pellet and gradually increase to full dose.

OTC - ACTIVE INGREDIENT SECTION

Equal parts of Hydrastis canadensis 6x, Thuja occidentalis 6x, Agnus castus 15x, Aralia quinquefolia 15x, Baryta carbonica 15x, Berberis vulgaris 15x, Bryonia 15x, Caladium seguinum 15x, Cantharis 15x, Causticum 15x, Chelidonium majus 15x, Cinchona officinalis 15x, Conium maculatum 15x, Gaultheria procumbens 15x, Graphites 15x, Kali carbonicum 15x, Lycopodium clavatum 15x, Nux vomica 15x, Onosmodium virginianum 15x, Phosphorus 15x, Sabal serrulata 15x, Selenium metallicum 15x, Sepia 15x, Silicea 15x, Staphysagria 15x.

OTC - PURPOSE SECTION

Formulated for associated symptoms such as decreased desire, dryness, anxiety and hypersexuality.

INACTIVE INGREDIENT SECTION

Inactive Ingredients: Gluten-free, non-GMO, organic beet-derived sucrose (lactose-free) pellets.

QUESTIONS SECTION

newtonlabs.net – Questions? 800.448.7256

Newton Laboratories, Inc. FDA Est # 1051203 - Conyers, GA 30013

WARNINGS SECTION

WARNINGS: Keep out of reach of children. Do not use if tamper-evident seal is broken or missing. If symptoms worsen or persist for more than a few days, consult a doctor. If pregnant or breast-feeding, ask a doctor before use.

OTC - PREGNANCY OR BREAST FEEDING SECTION

If pregnant or breast-feeding, ask a doctor before use.

OTC - KEEP OUT OF REACH OF CHILDREN SECTION

Keep out of reach of children.